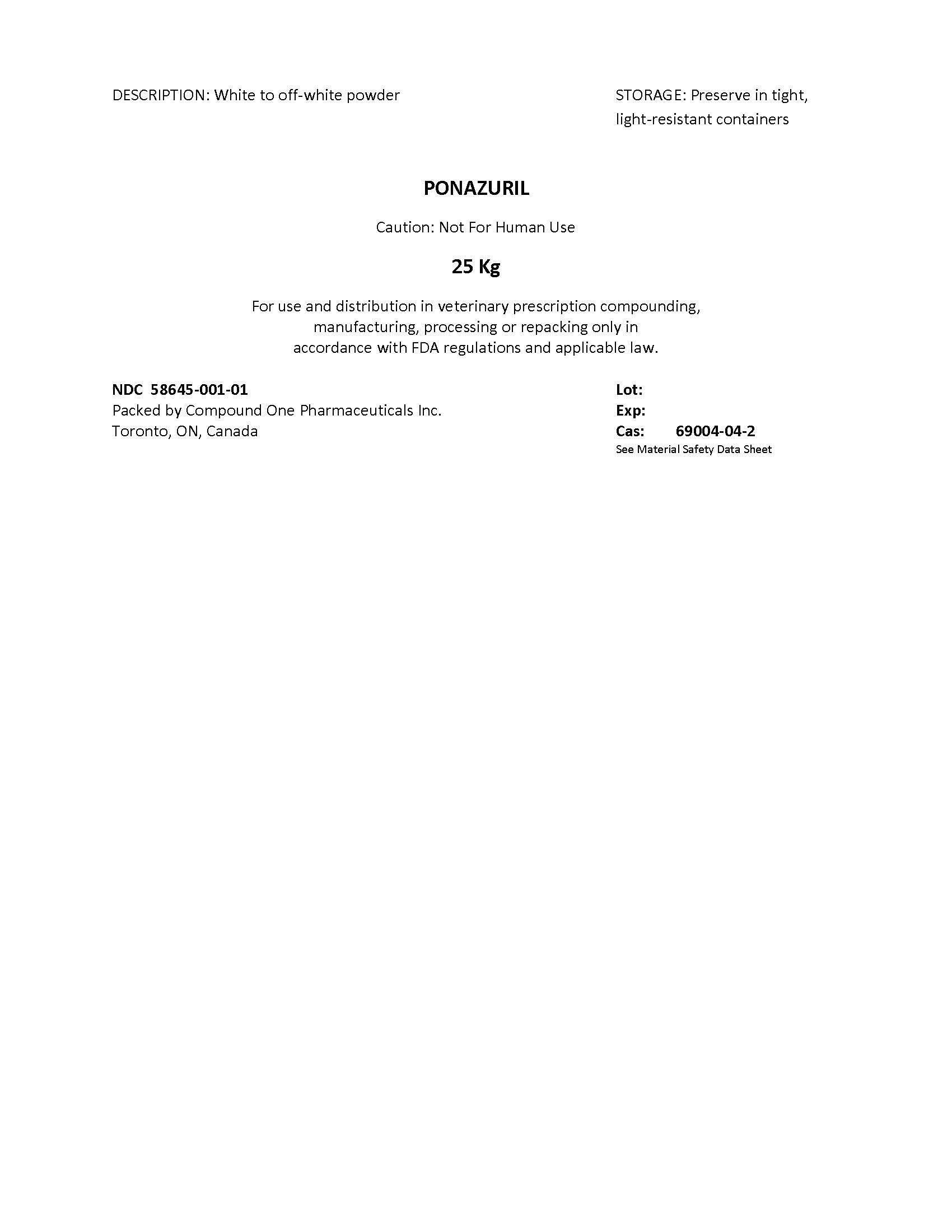 DRUG LABEL: PONAZURIL
NDC: 58645-001 | Form: POWDER
Manufacturer: Compound One Pharmaceuticals Inc.
Category: other | Type: BULK INGREDIENT
Date: 20131016

ACTIVE INGREDIENTS: PONAZURIL 1 g/1 g

Drug Facts